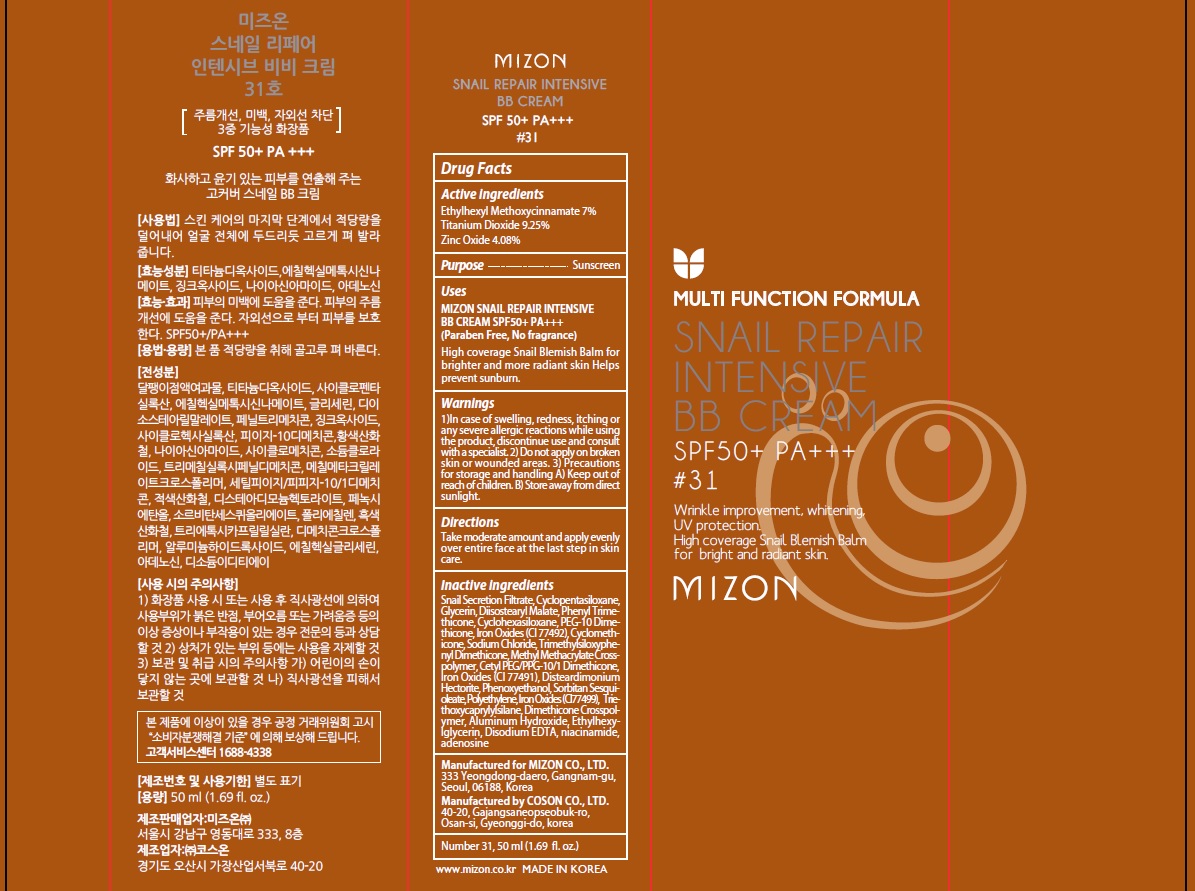 DRUG LABEL: MIZON SNAIL REPAIR INTENSIVE BB 31
NDC: 57718-370 | Form: CREAM
Manufacturer: MIZON CO.,LTD.
Category: otc | Type: HUMAN OTC DRUG LABEL
Date: 20180807

ACTIVE INGREDIENTS: Octinoxate 3.50 g/50 mL; Titanium Dioxide 4.62 g/50 mL; Zinc Oxide 2.04 g/50 mL
INACTIVE INGREDIENTS: Glycerin; Diisostearyl Malate

ACTIVE INGREDIENT

Active ingredients: Ethylhexyl Methoxycinnamate 7%, Titanium Dioxide 9.25%, Zinc Oxide 4.08%

INACTIVE INGREDIENT

Inactive ingredients:

Snail Secretion Filtrate, Cyclopentasiloxane, Glycerin, Diisostearyl Malate, Phenyl Trimethicone, Cyclohexasiloxane, PEG-10 Dimethicone, Iron Oxides (CI 77492), Cyclomethicone, Sodium Chloride, Trimethylsiloxyphenyl Dimethicone, Methyl Methacrylate Crosspolymer, Cetyl PEG/PPG-10/1 Dimethicone, Iron Oxides (CI 77491), Disteardimonium Hectorite, Phenoxyethanol, Sorbitan Sesquioleate, Polyethylene, Iron Oxides (CI 77499), Triethoxycaprylylsilane, Dimethicone Crosspolymer, Aluminum Hydroxide, Ethylhexylglycerin, Disodium EDTA, niacinamide, adenosine

PURPOSE

Purpose: Sunscreen

WARNINGS

1)In case of swelling, redness, itching or any severe allergic reactions while using the product, discontinue use and consult with a specialist.

2) Do not apply on broken skin or wounded areas.

3) Precautions for storage and handling A) Keep out of reach of children. B) Store away from direct sunlight.

DESCRIPTION

Uses:

MIZON SNAIL REPAIR INTENSIVE BB CREAM SPF50+ PA+++(Paraben Free, No fragrance)

High coverage Snail Blemish Balm for brighter and more radiant skin

Helps prevent sunburn

Directions:

Take moderate amount and apply evenly over entire face at the last step in skin care.